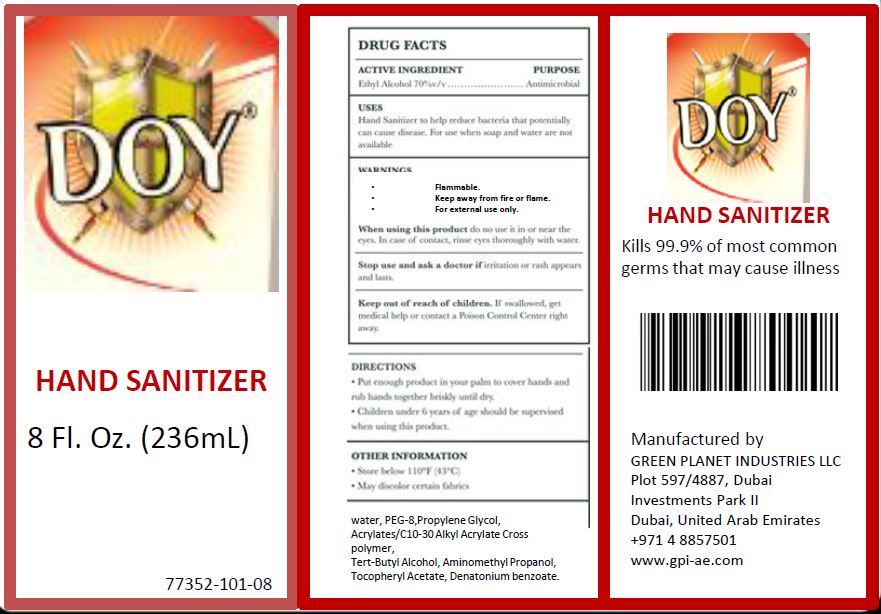 DRUG LABEL: HAND SANITIZER
NDC: 77352-101 | Form: GEL
Manufacturer: GREEN PLANET INDUSTRIES
Category: otc | Type: HUMAN OTC DRUG LABEL
Date: 20211213

ACTIVE INGREDIENTS: ALCOHOL 70 mL/100 mL
INACTIVE INGREDIENTS: WATER; POLYETHYLENE GLYCOL 400; PROPYLENE GLYCOL; CARBOMER INTERPOLYMER TYPE A (ALLYL SUCROSE CROSSLINKED); TERT-BUTYL ALCOHOL; AMINOMETHYLPROPANOL; .ALPHA.-TOCOPHEROL ACETATE; DENATONIUM BENZOATE

HAND SANITIZER GEL - 70% ALCOHOL - 77352-101

ACTIVE INGREDIENT

ETHYL ALCOHOL (70% w/v)

PURPOSE

ANTIMICROBIAL

USES

HAND SANITIZER TO HELP REDUCE BACTERIA THAT CAN POTENTIALLY CAUSE DISEASE. FOR USE WHEN SOAP AND WATER ARE NOT AVAILABLE.

WARNINGS

- FLAMMABLE.
- KEEP AWAY FROM FIRE OR FLAME.
- FOR EXTERNAL USE ONLY.

When using this product do not use it in or near the eyes. In case of contact, rinse eyes thoroughly with water.

Stop use and ask a doctor if irritation or rash appears and lasts.

KEEP OUT OF REACH OF CHILDREN. IF SWALLOWED, GET MEDICAL HELP OR CONTACT A POISON CONTROL CENTER RIGHT AWAY.

DIRECTIONS

- Put enough product in your palm to cover hands and rub hands together briskly until dry.
- Children under 6 years of age should be supervised when using this product.

OTHER INFORMATION

- Store below 110°F (43°C)
- May discolor certain fabrics.

INACTIVE INGREDIENTS

WATER, PEG-8, PROPYLENE GLYCOL, ACRYLATES/C10-30 ALKYL ACRYLATE CROSSPOLYMER, TERT-BUTYL ALCOHOL, AMINOMETHYL PROPANOL, TOCOPHERYL ACETATE, DENATONIUM BENZOATE.